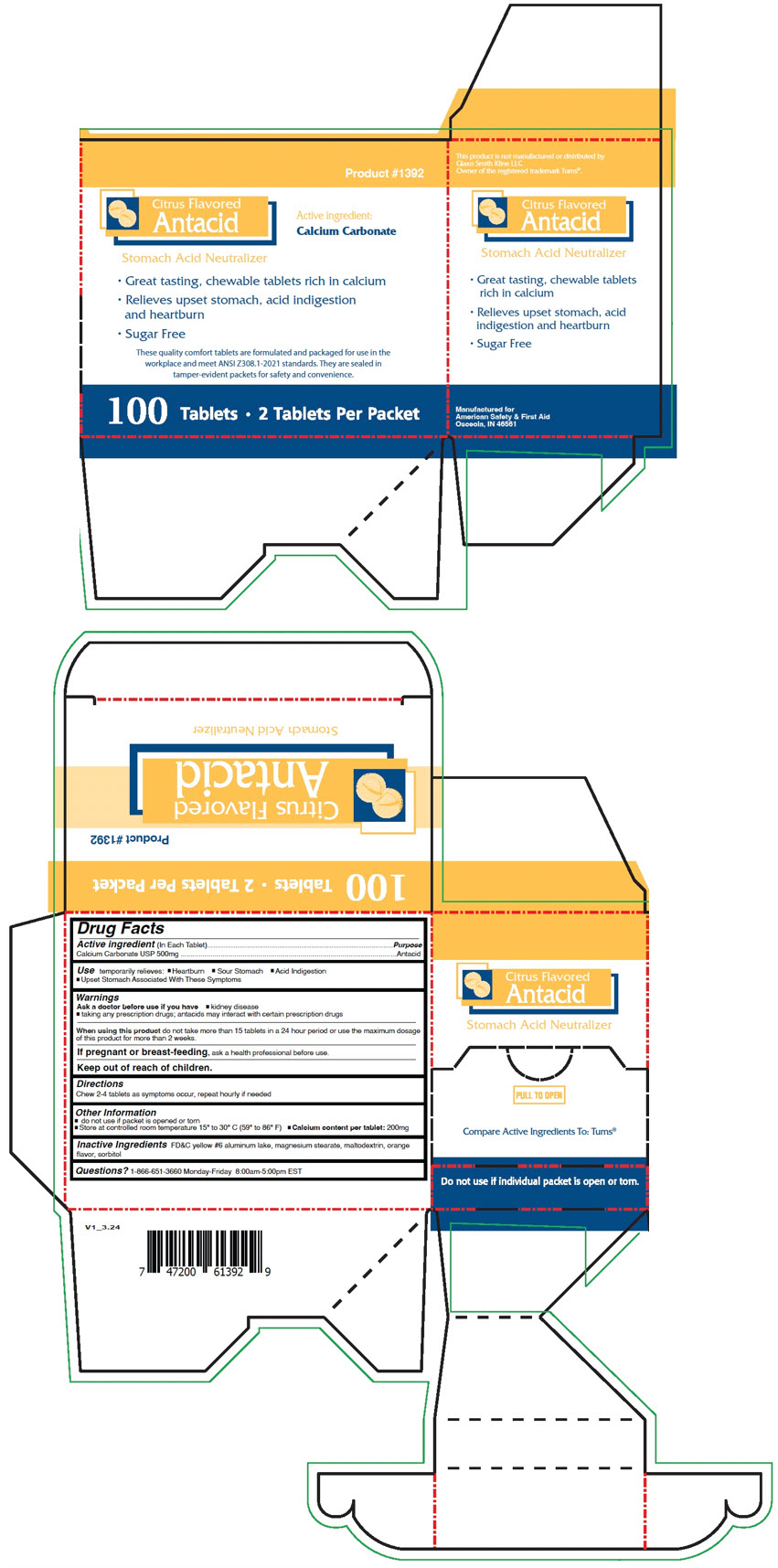 DRUG LABEL: Citrus Flavored Antacid
NDC: 73598-1392 | Form: TABLET, CHEWABLE
Manufacturer: JHK DBA American Safety & First Aid
Category: otc | Type: HUMAN OTC DRUG LABEL
Date: 20241015

ACTIVE INGREDIENTS: Calcium Carbonate 500 mg/1 1
INACTIVE INGREDIENTS: FD&C YELLOW NO. 6 ALUMINUM LAKE; magnesium stearate; maltodextrin; sorbitol

Citrus Flavored Antacid

Drug Facts

Active ingredient (In Each Tablet)

Calcium Carbonate USP 500mg

Purpose

Antacid

Use

temporarily relieves:

- Heartburn
- Sour Stomach
- Acid Indigestion
- Upset Stomach Associated With These Symptoms

Warnings

Ask a doctor before use if you have

- kidney disease
- taking any prescription drugs; antacids may interact with certain prescription drugs

When using this product do not take more than 15 tablets in a 24 hour period or use the maximum dosage of this product for more than 2 weeks.

PREGNANCY OR BREAST FEEDING

If pregnant or breast-feeding, ask a health professional before use.

Keep out of reach of children.

Directions

Chew 2-4 tablets as symptoms occur, repeat hourly if needed

Other Information

- do not use if packet is opened or torn
- Store at controlled room temperature 15° to 30° C (59° to 86° F)
- Calcium content per tablet: 200mg

Inactive Ingredients

FD&C yellow #6 aluminum lake, magnesium stearate, maltodextrin, orange flavor, sorbitol

Questions?

1-866-651-3660 Monday-Friday 8:00am-5:00pm EST

PRINCIPAL DISPLAY PANEL - 100 Tablet Packet Carton

Product #1392

Citrus Flavored
Antacid

Active ingredient:
Calcium Carbonate

Stomach Acid Neutralizer

- Great tasting, chewable tablets rich in calcium
- Relieves upset stomach, acid indigestion
  and heartburn
- Sugar Free

These quality comfort tablets are formulated and packaged for use in the
workplace and meet ANSI Z308.1-2021 standards. They are sealed in
tamper-evident packets for safety and convenience.

100 Tablets • 2 Tablets Per Packet